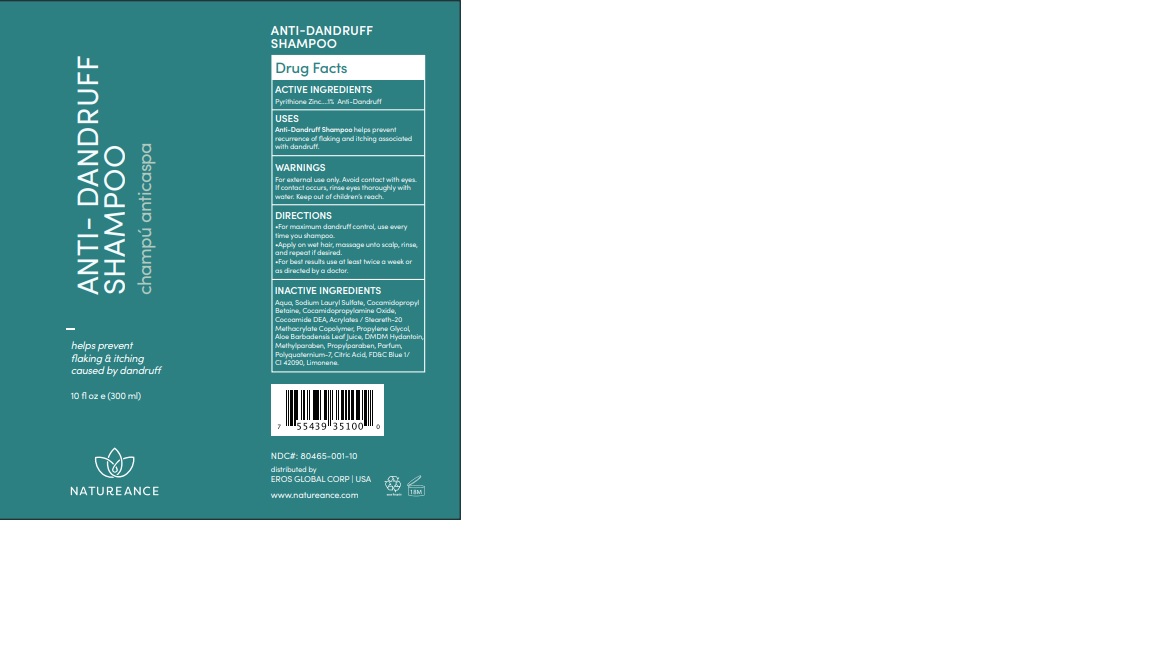 DRUG LABEL: PYRITHIONE ZINC
NDC: 80465-001 | Form: SHAMPOO
Manufacturer: EROS GLOBAL CORP
Category: otc | Type: HUMAN OTC DRUG LABEL
Date: 20220629

ACTIVE INGREDIENTS: PYRITHIONE ZINC 2 g/100 g
INACTIVE INGREDIENTS: WATER; ETHYL ACRYLATE/METHACRYLIC ACID/STEARETH-20 METHACRYLATE COPOLYMER; DMDM HYDANTOIN; PROPYLPARABEN; PHOSPHORIC ACID; LIMONENE, (+/-)-; BASIC BLUE 1; COCAMIDOPROPYLAMINE OXIDE; COCAMIDOPROPYL BETAINE; METHYLPARABEN; SODIUM LAURYL SULFATE

80465-001-10

DOSAGE AND ADMINISTRATION

For maximum dandruff control, use every time you shampoo.
Wet hair, massage unto scalp, rinse, and repeat if desired.

For best results use at least twice a week or as directed by a doctor.

WARNINGS

For external use only. Avoid contact with eyes. If contact occurs, rinse eyes thoroughly with water.

INACTIVE INGREDIENT

Aqua, Sodium Lauryl Sulfate, Cocamidopropyl Betaine, Cocamidopropylamine Oxide, Cocoamide DEA, Acrylates/Steareth-20 Methacrylate Copolymer, Propylene Glycol, Aloe Barbadensis Leaf Juice, DMDM Hydantoin, Methylparaben, Propylparaben, Parfum, Polyquaternium-7, Phosphoric Acid, FD&C Blue 1/ CI 42090, Limonene.

INDICATIONS AND USAGE

Anti-Dandruff Shampoo Helps prevent recurrence of flaking and itching associated with dandruff.

Keep Out of children’s reach.

PURPOSE

Anti-dandruff

ACTIVE INGREDIENT

Pyrithione Zinc 1%